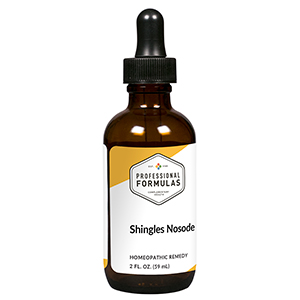 DRUG LABEL: Shingles Nosode
NDC: 63083-4028 | Form: LIQUID
Manufacturer: Professional Complementary Health Formulas
Category: homeopathic | Type: HUMAN OTC DRUG LABEL
Date: 20190815

ACTIVE INGREDIENTS: ECHINACEA ANGUSTIFOLIA WHOLE 6 [hp_X]/59 mL; LYSINE 6 [hp_X]/59 mL; DAPHNE MEZEREUM BARK 6 [hp_X]/59 mL; TOXICODENDRON PUBESCENS LEAF 6 [hp_X]/59 mL; SODIUM CHLORIDE 6 [hp_X]/59 mL; CROTON TIGLIUM SEED 8 [hp_X]/59 mL; HUMAN HERPESVIRUS 1 200 [hp_X]/59 mL; RECOMBINANT VARICELLA ZOSTER VIRUS GLYCOPROTEIN E ANTIGEN 200 [hp_X]/59 mL; HUMAN VARICELLA-ZOSTER IMMUNE GLOBULIN 200 [hp_X]/59 mL
INACTIVE INGREDIENTS: ALCOHOL; WATER

N28

ACTIVE INGREDIENTS

Echinacea angustifolia 6X
L-Lysine 6X
Mezereum 6X
Rhus toxicodendron 6X
Natrum muriaticum 6X, 30X
Croton tiglium 8X
Herpes simplex 200X
Herpes zoster 200X
Varicella 200X

QUESTIONS

Professional Formulas

PO Box 2034 Lake Oswego, OR 97035

INDICATIONS

For the temporary relief of fatigue or itchy, painful, or red skin.*

PURPOSE

*Claims based on traditional homeopathic practice, not accepted medical evidence. Not FDA evaluated.

WARNINGS

Consult a doctor if condition worsens or if symptoms persist. Keep out of the reach of children. In case of overdose, get medical help or contact a poison control center right away. If pregnant or breastfeeding, ask a healthcare professional before use.

Keep out of the reach of children.

PREGNANCY OR BREAST FEEDING

If pregnant or breastfeeding, ask a healthcare professional before use.

DIRECTIONS

Place drops under tongue 30 minutes before/after meals. Adults and children 12 years and over: Take 10 to 15 drops once weekly or monthly. If mild symptoms are present, take 10 drops up to 3 times per day. Consult a physician for use in children under 12 years of age.

OTHER INFORMATION

Tamper resistant. If seal is broken, do not use. After opening, close container tightly and store at room temperature away from heat.

INACTIVE INGREDIENTS

20% ethanol, purified water.

LABEL

Est 1985

Professional Formulas

Complementary Health

Shingles Nosode

Homeopathic Remedy

2 FL. OZ. (59 mL)